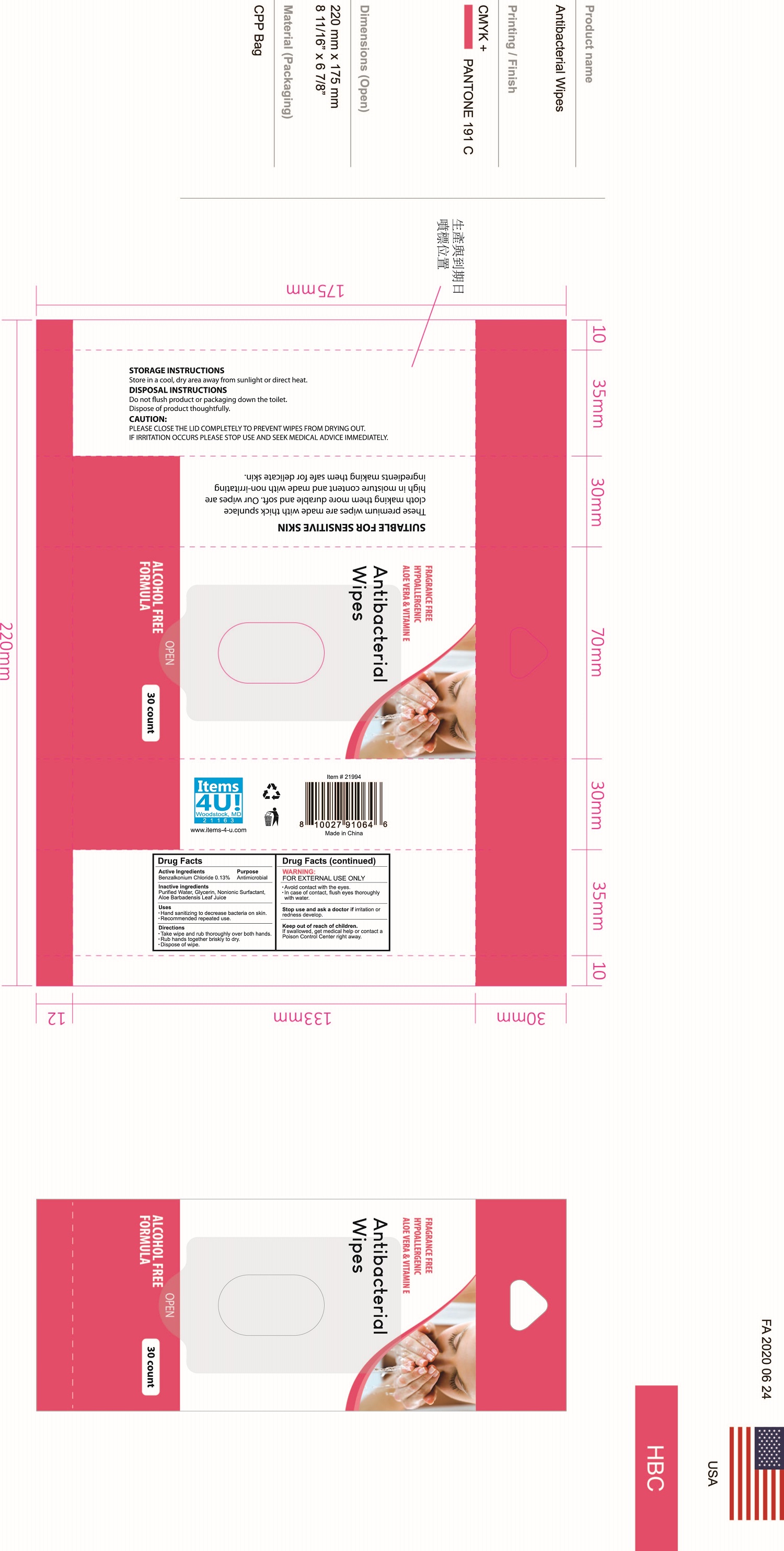 DRUG LABEL: Antibacterial Wet Wipes
NDC: 73326-002 | Form: SWAB
Manufacturer: Jacent Strategic Merchandising, LLC.
Category: otc | Type: HUMAN OTC DRUG LABEL
Date: 20200628

ACTIVE INGREDIENTS: BENZALKONIUM CHLORIDE 0.13 g/100 g
INACTIVE INGREDIENTS: WATER; GLYCERIN; GOSSYPIUM BARBADENSE LEAF; POLYSORBATE 20; METHYLISOTHIAZOLINONE; METHYLCHLOROISOTHIAZOLINONE

Antibacterial Wet Wipes

Active ingredient

benzalkonium chloride 0.13%

Purpose

Antibacterial

Uses

for hand sanitizing to decrease bacteria on the skin

recommended for repeated use

Warnings

For External use only.
Do not use if you are allergic to any of the ingredients.
When using this product avoid contact with the eyes,in case of contact, flush eyes thoroughly with water.
Stop use and ask a doctor if irritation or redness develop .

keep out of reach of children .if swallowed, get medical help or contact a Poison Control Center right away.

Directions

take wipe and rub thoroughly over all surfaces ofboth hands
·rub hands together briskly to dry·dispose of wipe

INACTIVE INGREDIENT

WATER PROPYLENE GLYCOL OCTHILINONE .ALPHA.-TOCOPHEROL